DRUG LABEL: Enema
NDC: 50730-2113 | Form: ENEMA
Manufacturer: H and P Industries, Inc. dba Triad Group
Category: otc | Type: HUMAN OTC DRUG LABEL
Date: 20091103

ACTIVE INGREDIENTS: mineral oil 118 mL/118 mL

Drug Facts

Active ingredient

Mineral Oil, 100%

Purpose

Lubricant Laxative

Use

- For relief of occasional constipation. This product generally produced bowel movement in 2 to 15 minutes.

Warnings

For rectal use only.

Do not use

- If you have abdominal pain, nausea, or vomiting, unless directed by a doctor.
- Longer than one week unless directed by a doctor.
- More than one enema per day unless directed by a doctor.

Ask a doctor before use

- if you have noticed a sudden change in bowel habits that persist over a period of 2 weeks

Stop use and ask a doctor if

- use results in unusual pain or other side effects.
- you have rectal bleeding or failure to have a bowel movement after use of a laxative. This may indicate a serious condition.

If pregnant or breastfeeding,

ask a health professional before use.

Keep out of reach of children

If swallowed, get medical help or contact a Poison Control Center right away.

Directions

Single Daily Dose
Do not use more unless directed by a doctor.
See Warnings.

Adults and children 12 years and older | One bottle (4 oz.) 120 mL delivered dose
Children 2 years to 12 years old | 1/2 Adult dose (2 oz.) 60 mL delivered dose
Children under 2 years of age | Ask a doctor

Dosage:

- Adults and children 12 years of age and older: rectal enema dosage is 120 milliliters in a single daily dose.
- Children 2 to 12 years of age: rectal enema dosage is 60 mililiters in a single daily dose, 1/2 of a bottle. (Children's dose of 60 mililiters can be measured by removing mineral oil from the bottle until the words "Mineral Oil" on the front face of the bottle are just covered).
- Children under 2 years of age: ask a doctor.

Directions for inserting enema
Positioning:
Left side position: Lie on left side with right knee bent and arms resting comfortably.
Knee chest position: Kneel, lower head and chest forward until left side of the face is resting on surface with arms resting comfortably.
CAUTION: Remove orange protective shield before inserting. To do so, hold bottle upright with one hand and pull gently to remove.

- with steady pressure, gently insert enema tip into rectum with a side to side movement with tip pointing toward navel.
- stop using if tip is hard to insert. Forcing tip into the rectum can cause injury (especially if you have hemorrhoids). If enema tip causes rectal bleeding or pain, get immediate medical care.
- Squeeze bottle until nearly all the liquid is released. Remove from rectum. Maintain position until urge to evacuate is strong (usually 1 to 5 minutes). If no urge is felt after 5 minutes of using, try to empty bowel. Call a doctor promptly if no liquid comes out of the rectum after 30 minutes because dehydration could occur.

Other Information

This product does not contain Dry Natural Rubber or Natural Rubber Latex.

Principal Display Panel

TRIAD
Ready-To-Use
MINERAL OIL
enema, USP
protective shield prevents contamination
lubricated tip assures ease of insertion
one way safety valve prevents reflux
easy to grip and squeeze bottle
carton sealed for safety
4 1/2 fl. oz. (133 ml)
CAT. No. 10-2113
Triad Disposables
Brookfield, WI 53045